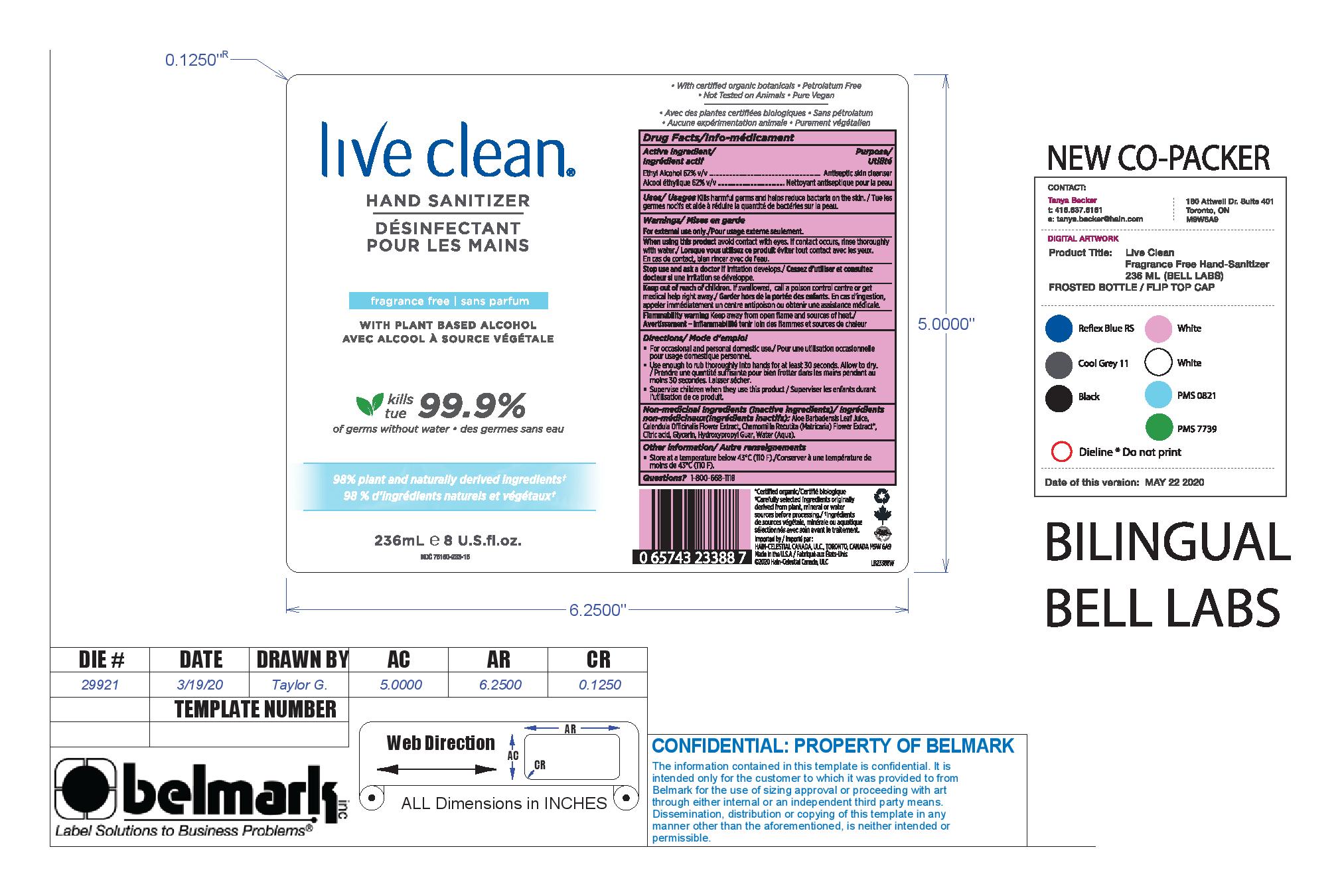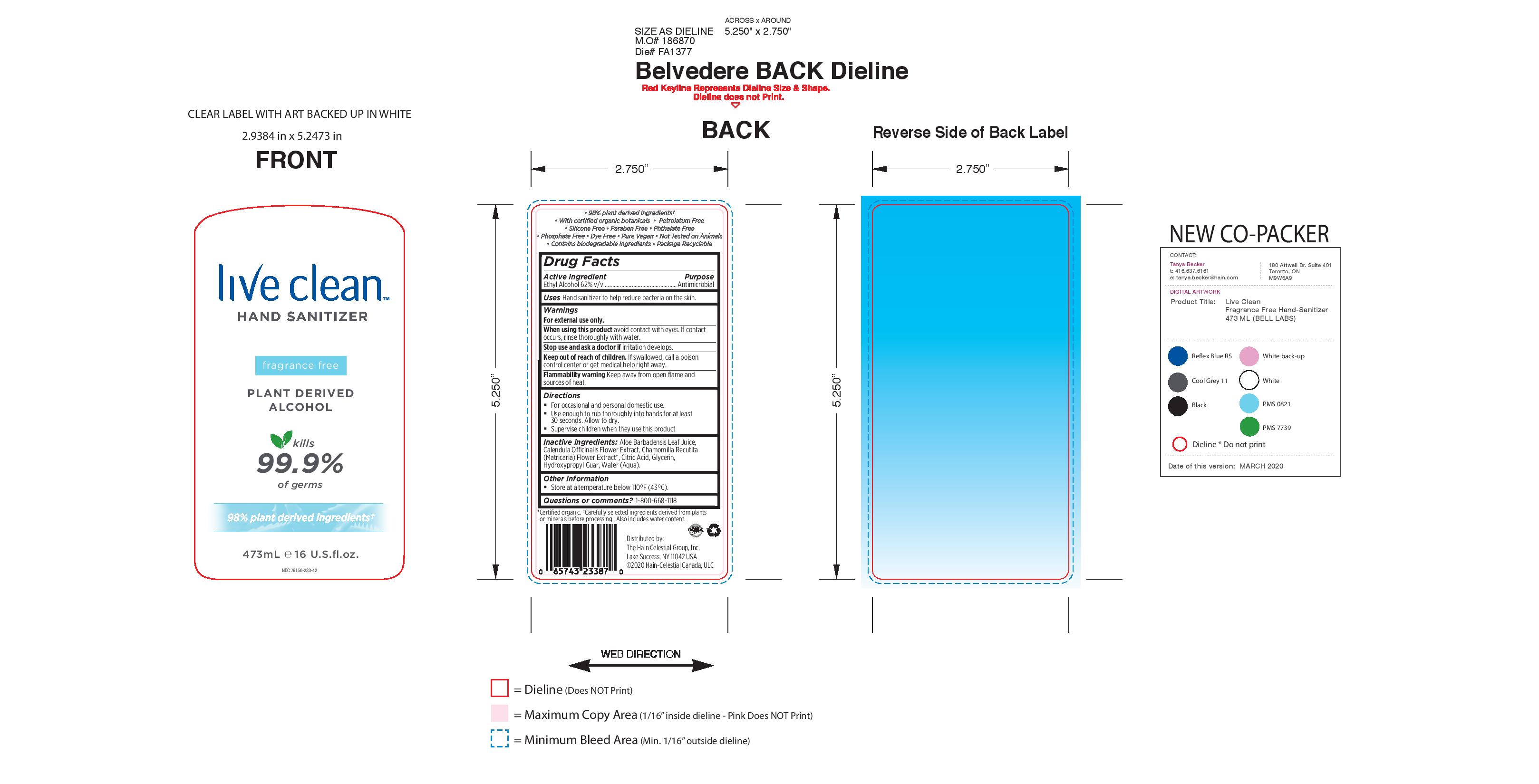 DRUG LABEL: Live Clean
NDC: 76150-233 | Form: LIQUID
Manufacturer: Bell International Laboratories, Inc
Category: otc | Type: HUMAN OTC DRUG LABEL
Date: 20200522

ACTIVE INGREDIENTS: ALCOHOL 62 mL/100 mL
INACTIVE INGREDIENTS: CITRIC ACID MONOHYDRATE; CALENDULA OFFICINALIS FLOWER; ALOE VERA LEAF; GUARAPROLOSE (1300 MPA.S AT 1%); WATER; CHAMOMILE; GLYCERIN

Hain Celestial 62% Hand Sanitizer Gel Unscented

Active Ingredient

Ethyl Alcohol 62% v/v

Purpose

Antimicrobial

Uses

Hand sanitizer to help reduce bacteria on the skin

Warnings

For external use only

When using this product avoid contact with eyes. If contact occurs, rinse thoroughly with water.

Stop use and ask a docutor if irritation develops

Flammability warning Keep away from open flame and sources of heat

Keep out of reach of children. If swallowed, call a poison control center or get medical help right away.

Directions

For occasional and personal domestic use

Use enough to rub thoroughly into hands for at least 30 seconds. Allow to dry

Supervise children when they use this product.

Inactive ingredient

Aloe Barbadensis Leaf Juice, Calendula Officinalis Flower Extrat, Chamomilla Recutita (Matricaria) Flower Extract, Citric Acid, Glycerin, Hydroxypropyl Guar, Water (Aqua)

Other Information

Store at temperatures below 110 F (43 C)

Questions or comments?

1-800-668-1118